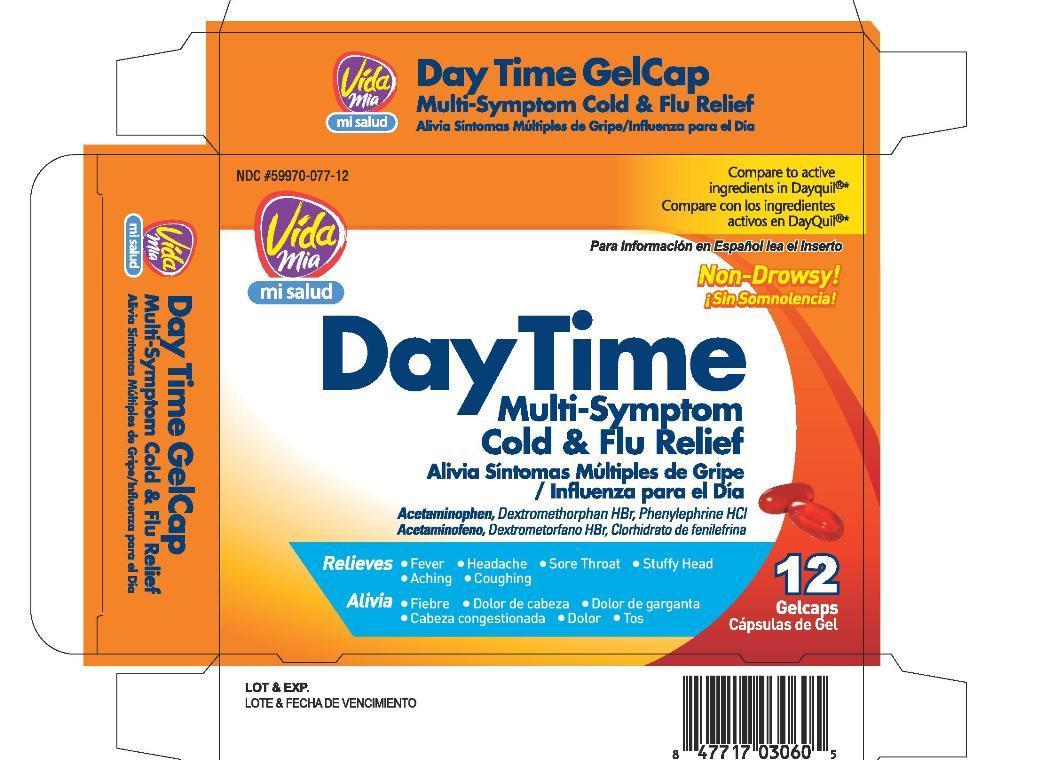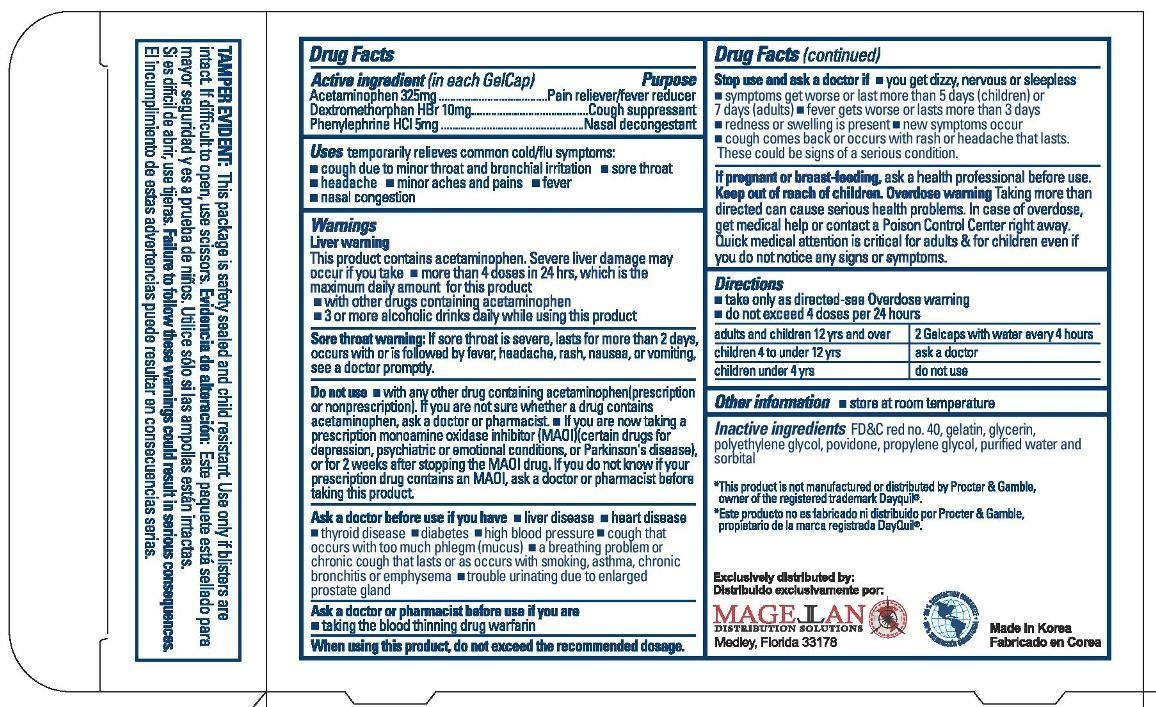 DRUG LABEL: Day Time Gelcap
NDC: 59970-077 | Form: CAPSULE, LIQUID FILLED
Manufacturer: Navarro Discount Pharmacies,LLC
Category: otc | Type: HUMAN OTC DRUG LABEL
Date: 20130118

ACTIVE INGREDIENTS: ACETAMINOPHEN 325 mg/1 1; DEXTROMETHORPHAN HYDROBROMIDE 10 mg/1 1; PHENYLEPHRINE HYDROCHLORIDE 5 mg/1 1
INACTIVE INGREDIENTS: FD&C RED NO. 40; GELATIN; GLYCERIN; POLYETHYLENE GLYCOLS; POVIDONE; PROPYLENE GLYCOL; WATER; SORBITOL

Drug Facts

Active ingredients(in each GelCap)

Acetaminophen 325mg

Dextromethorphan HBr 10mg

Phenylephrine HCl 5mg

Purpose

Pain reliever/fever reducer

Cough suppressant

Nasal decongestant

Uses

temporarily relieves common cold/flu symptoms:

- cough due to minor throat and bronchial irritation
- sore throat
- headache
- minor aches and pains
- fever
- nasal congestion

Warnings

Liver Warning: This product contains acetaminophen. Severe liver damage may occur if you take

- more than 4 doses in 24 hrs, which is the maximum daily amount for this product
- with other drugs containing acetaminophen
- 3 or more alcoholic drinks daily while using this product

Sore Throat Warning: If sore throat is severe, persists for more than 2 days, is accompanied or followed by fever, headache, rash, nausea, or vomiting, consult a doctor promptly.

Do not use

- with any other drug containing acetaminophen(prescription or nonprescription). If you are not sure whether a drug contains acetaminophen, ask a doctor or pharmacist.
- if you are now taking a prescription monoamine oxidase inhibitor (MAOI)(certain drugs for depression, psychiatric or emotional conditions, or Parkinson's disease), or for 2 weeks after stopping the MAOI drug. If you do not know if your prescription drug contains an MAOI, ask a doctor or pharmacist before taking this product.

Ask a doctor before use if you have

- liver disease
- heart disease
- thyroid disease
- diabetes
- high blood pressure
- trouble urinating due to enlarged prostate gland
- cough that occurs with too much phegm(mucus)
- Persistent or chronic cough as occurs with smoking, asthma, emphysema

Ask a doctor or pharmacist before use if you are

taking the blood thinning drug warfarin.

Stop use and ask a doctor if

- you get nervous, dizzy or sleepless
- symptoms get worse or last more than 5 days (children) or 7 days (adults)
- fever gets worse or lasts more than 3 days
- redness or swelling is present
- new symptoms occur
- cough comes back or occurs with rash or headache that lasts. These could be signs of a serious condition.

If pregnant or breast-feeding,

ask a health professional before use.

Overdose warning:

Taking more than directed can cause serious health problems. In case of overdose, get medical help or contact a Poison Control Center right away. Quick medical attention is critical to adults and children even if you do not notice any signs or symptoms.

Directions

- take only as directed-see Overdose warning
- do not exceed 4 doses per 24 hours
  adults and children 12 yrs and over | 2 GelCaps with water every 4 hrs
  children 4 to under 12 yrs | ask a doctor
  children under 4 yrs | do not use

Other information

- store at room temperature

Inactive ingredients

FDC red no. 40, gelatin, glycerin, polyethylene glycol, povidone, propylene glycol, purified water and sobitol special

PACKAGE LABEL

Daytime gelcap